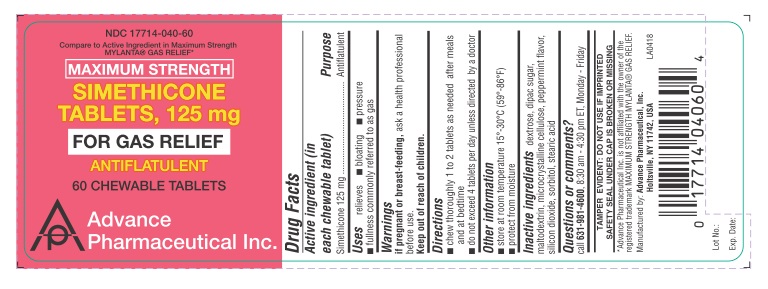 DRUG LABEL: Simethicone
NDC: 17714-040 | Form: TABLET, CHEWABLE
Manufacturer: Advance Pharmaceutical Inc.
Category: otc | Type: HUMAN OTC DRUG LABEL
Date: 20181217

ACTIVE INGREDIENTS: DIMETHICONE 125 mg/1 1
INACTIVE INGREDIENTS: DEXTROSE; SUCROSE; MICROCRYSTALLINE CELLULOSE; MALTODEXTRIN; PEPPERMINT; SILICON DIOXIDE; SORBITOL; STEARIC ACID

GAS RELIEF SIMETHICONE 125 MG

Active Ingredient

(in each chewable tablet)

Simethicone 125 mg

Purpose

Antiflatulent

Uses

relieves

- bloating
- pressure
- discomfort of gas which can be caused by certain foods or air swallowing

Warnings

If pregnant or breast-feeding, ask a health professional before use.

Keep out of reach of children

Directions

- chew thoroughly 1 to 2 tablets as needed after meals and at bed time.
- do not exceed 6 tablets per day unless directed by a physician

Other Information

- store at room temperature 15-30 °C (59-86 °F)
- protect from moisture

Inactive Ingredients

dextrose, dipac sugar, maltodextrin, microcrystalline cellulose, peppermint flavor, silicon dioxide, sorbitol, stearic acid

Questions or Comments

TAMPER EVIDENT: DO NOT USE IF IMPRINTED SAFETY SEAL UNDER CAP IS BROKEN OR MISSING

Call 631-981-4600, 8.30 am – 4.30 pm EST Monday - Friday

Package Label

NDC: 17714-040-60 – 60 CHEWABLE TABLETS